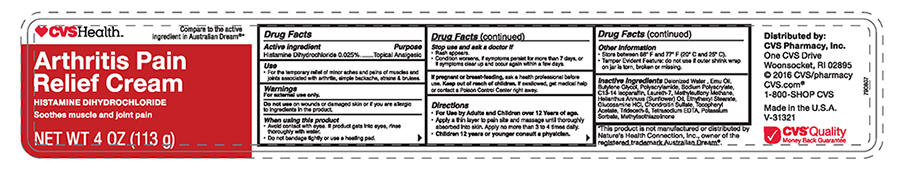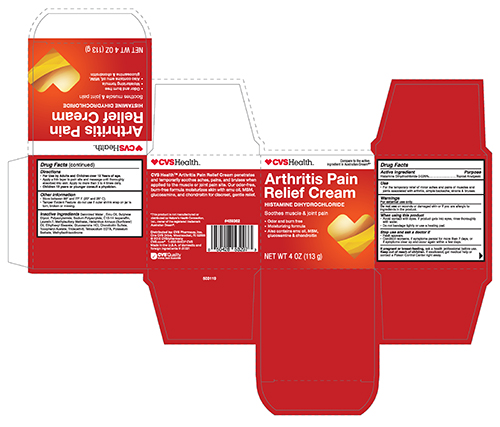 DRUG LABEL: CVS Arthritis Pain Relief
NDC: 69842-301 | Form: CREAM
Manufacturer: CVS Health
Category: otc | Type: HUMAN OTC DRUG LABEL
Date: 20241111

ACTIVE INGREDIENTS: HISTAMINE DIHYDROCHLORIDE .025 g/100 g
INACTIVE INGREDIENTS: WATER; EMU OIL; BUTYLENE GLYCOL; POLYACRYLAMIDE (1500 MW); SODIUM POLYACRYLATE (8000 MW); C13-14 ISOPARAFFIN; LAURETH-7; DIMETHYL SULFONE; HELIANTHUS ANNUUS FLOWERING TOP; ETHYLHEXYL STEARATE; GLUCOSAMINE HYDROCHLORIDE; CHONDROITIN SULFATE (SHARK); .ALPHA.-TOCOPHEROL ACETATE; TRIDECETH-6; EDETATE SODIUM; POTASSIUM SORBATE; METHYLISOTHIAZOLINONE

Drug facts

Active Ingredient

Histamine Dihydrochloride .025%

Purpose

Topical Analgesic

Use

For temporary relief of minor aches and pains of muscles and joints assited with arthritis, simple backache, strains & bruises.

Warnings

For external use only.

Do not use on wounds or damaged skin or if you are allergic to ingredients in the product.

When using this product

Avoid contact with eyes. If product gets inot eyes,rinse thoroughly with water.

Do not bandage tightly or use a heating pad.

Stop use and ask a doctor if

Rash appears.

Condition worsens, if symptoms persist for more than 7 days, or if symptoms clear up and occur again within a few days.

PREGNANCY OR BREAST FEEDING

If pregnant or breast-feeding, ask a health professional before use.

KEEP OUT OF REACH OF CHILDREN

Keep out of the reach of children. If swallowed, get medical help or contact a Poison Control Center right away.

Directions

For use by adults and Children over 12 years of age.

- apply a thin layer tp the pain site and massage until thoroughly absorbed into skin. Apply no more than 3 to 4 times daily.
- Children 12 years or younger consult a physician.

Other information

Store between 68° and 77° F (20° and 25° C)

Tamper evident feature:do not use if outer shrink wrap on jar is torn, broken or missing.

Inactive Ingredients

Deoinized Water, Emu Oil, Butylene Glycol, Polyacrylamide, Sodium Polyacrylate, C13-C14 Isoparaffin, Laureth-7, Methylsulfonylmethane, Hellanthus Annuus(Sunflower)Oil, Ethylhexyl Stearate, Glucosamine HCL, Chondroitin Sulfate, Tocopheryl Acetate, Trideceth-6, Tetrasodium EDTA, Potassium Sorbate, Methylisothiazolinone

CVS Arthritis Cream 4 oz-jar

CVS Health

Arthritis Pain Relief Cream

Histamine Dihydrochloride

Soothes muscle and joint pain

NET WT 4 oz (113g)

CVS Arthritis Cream 4 oz -Carton

CVS Health

Arthritis Pain Releif Cream

Histamine Dihydrochloride

Soothes muscle&joint pain

- Odor and burn free
- Moisturizing formula
- Also contains emu oil, MSM, glucosamine & chondroitin NET WT 4oz (113g)